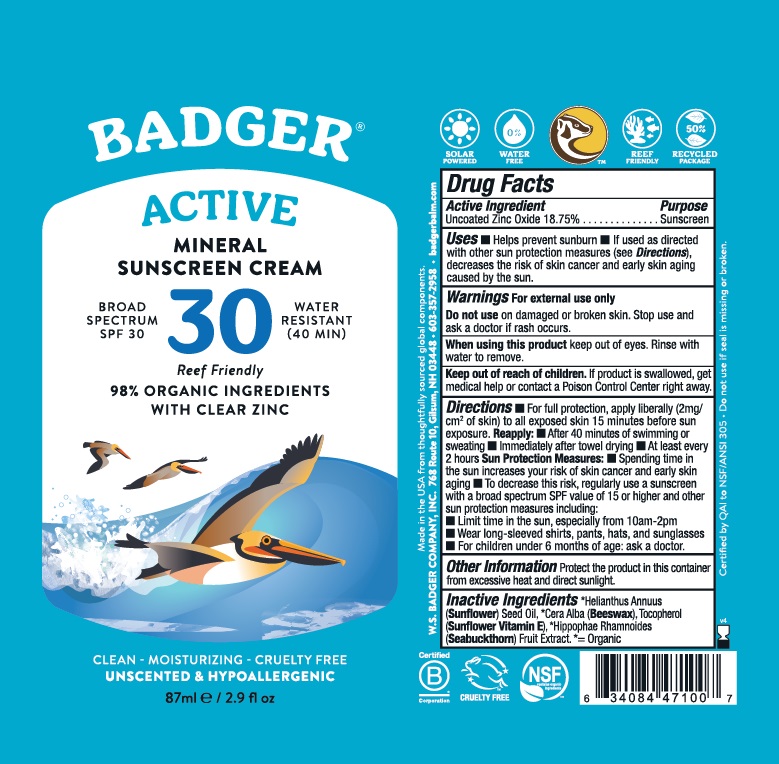 DRUG LABEL: Badger Active SPF 30 Mineral Sunscreen
NDC: 62206-3031 | Form: CREAM
Manufacturer: W.S. Badger Company, Inc.
Category: otc | Type: HUMAN OTC DRUG LABEL
Date: 20241231

ACTIVE INGREDIENTS: ZINC OXIDE 18.75 g/100 mL
INACTIVE INGREDIENTS: SUNFLOWER OIL; YELLOW WAX; TOCOPHEROL; HIPPOPHAE RHAMNOIDES FRUIT

Badger® Active Mineral Sunscreen Cream SPF 30

Drug Facts

Active Ingredient

Uncoated Zinc Oxide 18.75%

Purpose

Sunscreen

Uses

- Helps prevent sunburn
- If used as directed with other sun protection measures (see Directions), decreases the risk of skin cancer and early skin aging caused by the sun.

Warnings

For external use only

Do not use on damaged or broken skin. Stop and ask a doctor if rash occurs.

When using this product keep out of eyes. Rinse with water to remove.

Keep out of reach of children. If product is swallowed, get medical help or contact a Poison Control Center right away.

Directions

- For full protection, apply liberally (2mg/cm^2 of skin) to all exposed skin 15 minutes before sun exposure.

Reapply:

- After 40 minutes of swimming or sweating
- Immediately after towel drying
- At least every 2 hours

Sun Protection Measures:

- Spending time in the sun increases your risk of skin cancer and early skin aging
- To decrease this risk, regularly use a sunscreen with a broad spectrum SPF value of 15 or higher and other sun protection measures including:
  - Limit time in the sun, especially from 10am-2pm
  - Wear long-sleeved shirts, pants, hats, and sunglasses
- For children under 6 months of age: ask a doctor.

Ingredients

[= Organic] Helianthus Annuus (Sunflower) Oil, Cera Alba (Beeswax), Tocopherol (Sunflower Vitamin E), * Hippophae rhamnoides (Sea Buckthorn) Fruit Extract.

Other Information

Protect the product in this container from excessive heat and direct sunlight.

PRINCIPAL DISPLAY PANEL - 87 ml Tube Label

BADGER ®

Active

Mineral Sunscreen Cream
BROAD

SPECTRUM
SPF 30

WATER

RESISTANT (40 MIN)

98% ORGANIC INGREDIENTS

WITH CLEAR ZINC

CLEAN, MOISTURIZING, CRUELTY-FREE

UNSCENTED & HYPOALLERGENIC

SOLAR

POWERED

WATER

FREE

REEF

FRIENDLY

50%

RECYCLED

PACKAGE

87ml/2.9 fl.oz